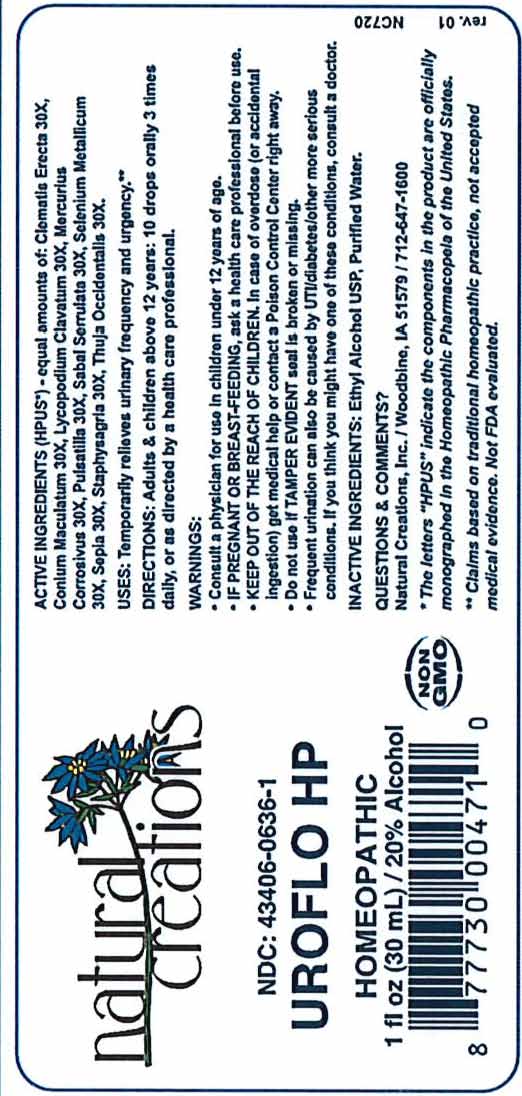 DRUG LABEL: Uroflo HP
NDC: 43406-0636 | Form: LIQUID
Manufacturer: Natural Creations, Inc
Category: homeopathic | Type: HUMAN OTC DRUG LABEL
Date: 20251218

ACTIVE INGREDIENTS: CLEMATIS RECTA FLOWERING TOP 30 [hp_X]/1 mL; CONIUM MACULATUM FLOWERING TOP 30 [hp_X]/1 mL; LYCOPODIUM CLAVATUM SPORE 30 [hp_X]/1 mL; MERCURIC CHLORIDE 30 [hp_X]/1 mL; PULSATILLA VULGARIS WHOLE 30 [hp_X]/1 mL; SAW PALMETTO 30 [hp_X]/1 mL; SELENIUM 30 [hp_X]/1 mL; SEPIA OFFICINALIS JUICE 30 [hp_X]/1 mL; DELPHINIUM STAPHISAGRIA SEED 30 [hp_X]/1 mL; THUJA OCCIDENTALIS LEAFY TWIG 30 [hp_X]/1 mL
INACTIVE INGREDIENTS: ALCOHOL; WATER

Uroflo HP

ACTIVE INGREDIENT

ACTIVE INGREDIENTS (*HPUS) - equal amounts of: Clematis Erecta 30X, Conium Maculatum 30X, Lycopodium Clavatum 30X, Mercurius Corrosivus 30X, Pulsatilla 30X, Sabal Serrulata 30X, Selenium Metallicum 30X, Sepia 30X, Staphysagria 30X, Thuja Occidentalis 30X

INDICATIONS AND USAGE

USES: Termporarily relieves urinary frequency and urgency.**

PURPOSE

USES: Termporarily relieves urinary frequency and urgency.**

DOSAGE AND ADMINISTRATION

DIRECTIONS: Adults & children above 12 years: 10 drops orally 3 times daily, or as directed by a health care professional.

KEEP OUT OF REACH OF CHILDREN

KEEP OUT OF THE REACH OF CHILDREN. In case of overdose (or accidental ingestion) get medical help or contact a Poison Control Center right away.

WARNINGS:

- Consult a physician for use in children under 12 years of age.
- IF PREGNANT OR BREAST-FEEDING, ask a health care professional before use.
- KEEP OUT OF THE REACH OF CHILDREN. In case of overdose (or accidental ingestion) get medical help or contact a Poison Control Center right away.
- Frequent urination can also be caused by UTI/diabetes/other more serius conditions. If you think you might have one of these conditions consult a doctor.
- Do not use if TAMPER EVIDENT seal is broken or missing.

INACTIVE INGREDIENTS: Ethyl Alcohol USP, Purified Water.

QUESTIONS & COMMENTS?

Natural Creations, Inc. / Woodbine, IA 51579 / 712-647-1600

REFERENCES

*The letters "HPUS" indicate the components in this product are officially monographed in the Homeopathic Pharmacopeia of the United States.

**Claims based on traditional homeopathic practice, not accepted medical evidence. Not FDA evaluated.

PACKAGE LABEL

NDC:43406-0636-1

Uroflo HP

HOMEOPATHIC

1 fl oz (30mL) / 20% Alcohol